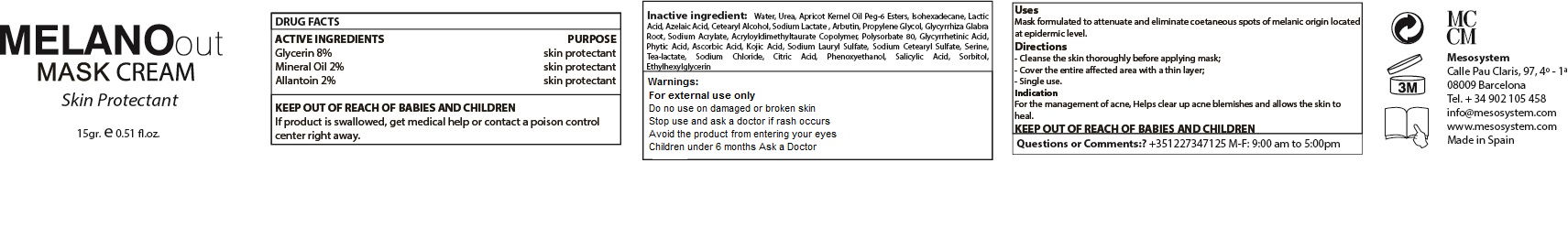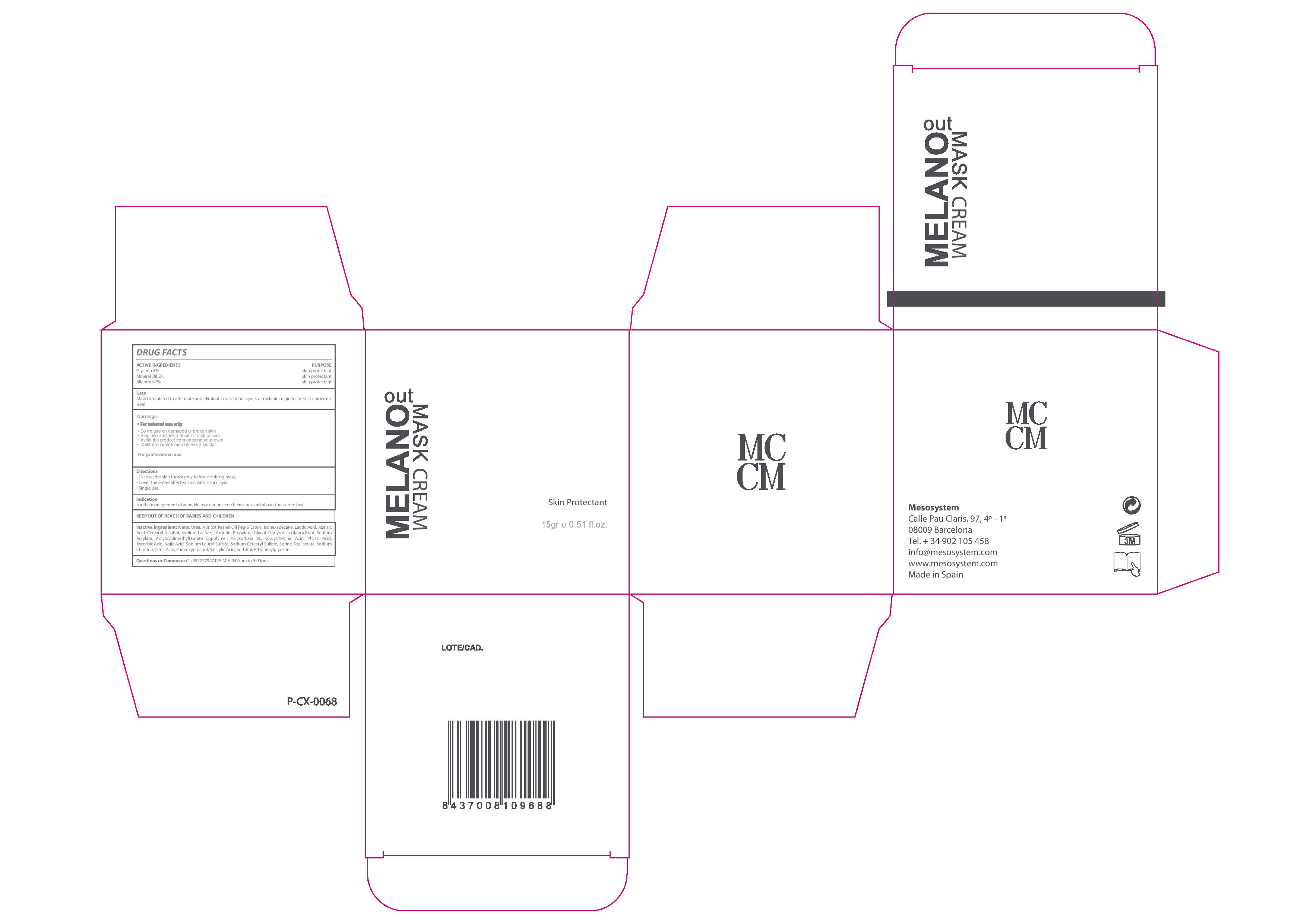 DRUG LABEL: Melano Out Mask
NDC: 70663-010 | Form: CREAM
Manufacturer: MESO SYSTEM S.A.
Category: otc | Type: HUMAN OTC DRUG LABEL
Date: 20161218

ACTIVE INGREDIENTS: GLYCERIN 8 mg/1 mL; ALLANTOIN 2 mg/1 mL; MINERAL OIL 2 mg/1 mL
INACTIVE INGREDIENTS: SORBITOL 0.1 mg/1 mL; ISOHEXADECANE 3 mg/1 mL; WATER 38.8 mg/1 mL; LACTIC ACID 3 mg/1 mL; PHENOXYETHANOL 0.9 mg/1 mL; ETHYLHEXYLGLYCERIN 0.1 mg/1 mL; APRICOT KERNEL OIL PEG-6 ESTERS 3 mg/1 mL; UREA HYDROCHLORIDE 8 mg/1 mL; AZELAIC ACID 2 mg/1 mL; ISOSTEARYL ALCOHOL 2 mg/1 mL; SODIUM LACTATE 2 mg/1 mL; ARBUTIN 2 mg/1 mL; PROPANEDIOL 2 mg/1 mL; GLYCYRRHIZA GLABRA 2 mg/1 mL; SODIUM ACRYLATE 2 mg/1 mL; SODIUM ACRYLATE/SODIUM ACRYLOYLDIMETHYLTAURATE COPOLYMER (4000000 MW) 2 mg/1 mL; POLYSORBATE 80 2 mg/1 mL; ENOXOLONE 2 meq/1 mL; FYTIC ACID 2 mg/1 mL; ASCORBIC ACID 2 mg/1 mL; KOJIC ACID 1 mg/1 mL; SODIUM LAURYL SULFATE 1 mg/1 mL; SODIUM CETOSTEARYL SULFATE 1 mg/1 mL; SERINE 1 mg/1 mL; TRIETHANOLAMINE LACTATE 1 mg/1 mL; SODIUM CHLORIDE 1 mg/1 mL; ANHYDROUS CITRIC ACID 1 mg/1 mL; SALICYLIC ACID 0.1 mg/1 mL

MELANO OUT MASK CREAM

Warnings

Stop use and ask a Doctor if rash occurs

WARNINGS

- For external use only.
- Do no use on damaged or broken skin
- Stop use and ask a doctor if rash occurs
- Avoid the product from entering your eyes
- Children under 6 months Ask a Doctor

USES

- Mask formulated to attenuate and eliminate coetanous spots of melanic origin located at epidemic levels.

- Keep out of the reach of chuldren.
- In case of overdose get medical help or Contact a Poison Control Center right away.

DIRECTIONS

- Clean the skin thoroughly before applying the mask
- Covered the entire skin with a thin layer
- Single use

QUESTIONS OR COMMENTS ?

- +35 1227347125 M-F: 9:00 am to 5:00 pm

ACTIVE INGREDIENTS

Active Ingredients Purpose

Glycerin 2%....................................Skin Protectant

Mineral Oil 2%................................Skin Protectant

Allantoin 2%...................................Skin Protectant

Inactive Ingredients

Water, Urea, Apricot Kernel Oil Peg-6 Esters, Isohexadecane, Lactic Acid, Azelaic Acid, Cetearyl Alcohol, Sodium Lactate, Arbutin, Propylene Glycol, Glycyrrhiza Glabra Root, Sodium Acrylate, Acryloyldimethyltaurate Copolymer, Polysorbate 80, Glycyrrhetinic Acid, Phytic Acid, Ascorbic Acid, Kojic Acid, Sodium Lauryl Sulfate, Sodium Cetearyl Sulfate, Serine, Tea-lactate, Sodium Chloride, Citric Acid, Phenoxyethanol, Salicylic Acid, Sorbitol, Ethylhexylglycerin

INDICATIONS AND USAGE

- Mask formulated to attenuate and eliminate coetanous spots of melanic origin located at epidemic levels.